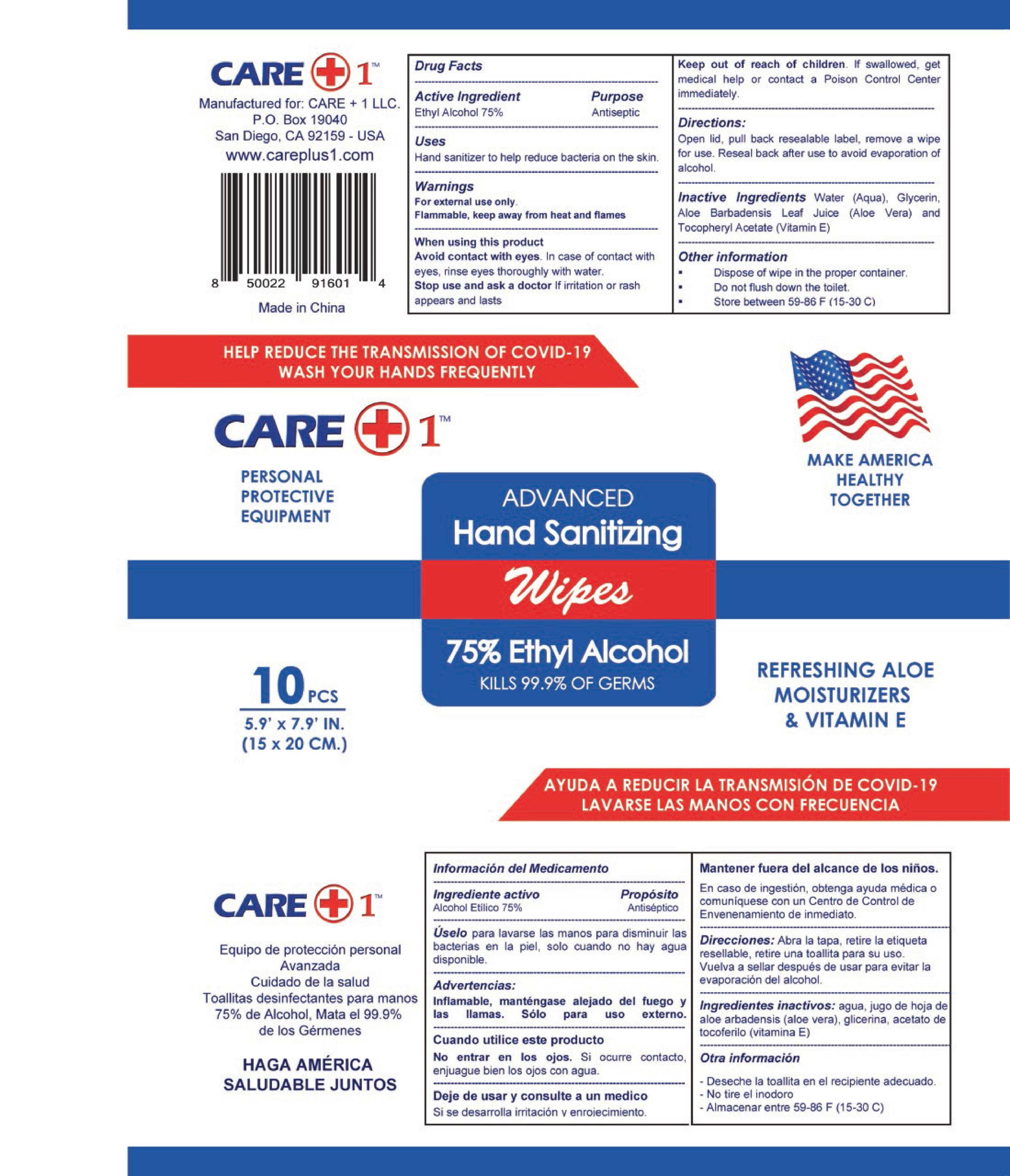 DRUG LABEL: CARE Plus 1 LLC
NDC: 79901-003 | Form: CLOTH
Manufacturer: Zhejiang Tianbo Daily Necessities Co. Ltd
Category: otc | Type: HUMAN OTC DRUG LABEL
Date: 20210219

ACTIVE INGREDIENTS: ALCOHOL 75 mL/100 mL
INACTIVE INGREDIENTS: GLYCERIN; ALOE VERA LEAF; WATER; .ALPHA.-TOCOPHEROL ACETATE, D-

This is a hand sanitizer manufactured according to the Temporary Policy for Preparation of Certain Alcohol-Based Hand Sanitizer Products During the Public Health Emergency (CoViD-19); Guidance for Industry.

The hand sanitizer is manufactured using only the following United States Pharmacopoeia (USP) grade ingredients in the preparation of the product (percentage in final product formulation) consistent with World Health Organization (WHO) recommendations:

1. Alcohol (ethanol) (USP or Food Chemical Codex (FCC) grade) (80%, volume/volume (v/v)) in an aqueous solution denatured according to Alcohol and Tobacco Tax and Trade Bureau regulations in 27 CFR part 20.
2. Glycerol (1.45% v/v).
3. Hydrogen peroxide (0.125% v/v).
4. Sterile distilled water or boiled cold water.

The firm does not add other active or inactive ingredients. Different or additional ingredients may impact the quality and potency of the product.

Active Ingredient(s)

Ethyl Alcohol 75% v/v.

Purpose

Antiseptic

Use

Hand Sanitizer to help reduce bacteria on the skin.

Warnings

For external use only. Flammable, keep away from heat and flames

When using this product avoid contact with eyes. In case of contact with eyes, rinse eyes thoroughly with water.
Stop use and ask a doctor if irritation or rash appears and lasts.

Stop use and ask a doctor if irritation or rash occurs. These may be signs of a serious condition.

Keep out of reach of children. If swallowed, get medical help or contact a Poison Control Center immediately.

Directions

Open lid, pull back resealable label, remove a wipe for use. Reseal back after use to avoid evaporation of alcohol.

Other information

- Dispose of wipe in the proper container.
- Do not flush down the toilet.
- Store between 59-86F (15-30C)

Inactive ingredients

Water (aqua), Glycerin, Aloe Barbadensis Leaf Juice (Alose Vera) and Tocopheryl Acetate (Vitamin E)